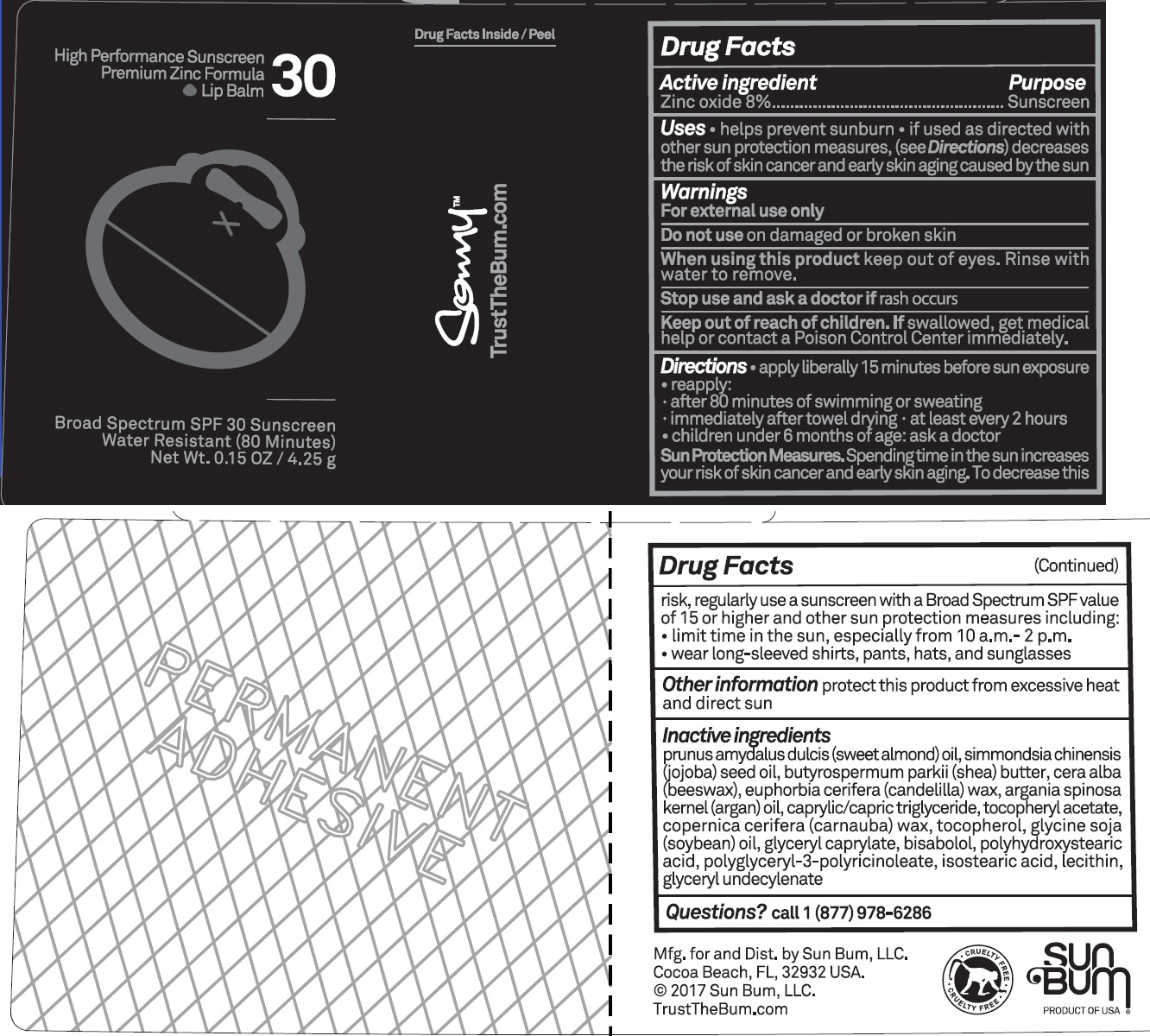 DRUG LABEL: Sun Bum Signature SPF 30 Sunscreen Lip Balm
NDC: 69039-277 | Form: STICK
Manufacturer: Sun Bum, LLC
Category: otc | Type: HUMAN OTC DRUG LABEL
Date: 20220204

ACTIVE INGREDIENTS: ZINC OXIDE 80 mg/1 g
INACTIVE INGREDIENTS: ALMOND OIL; JOJOBA OIL; SHEA BUTTER; WHITE WAX; CANDELILLA WAX; ARGAN OIL; MEDIUM-CHAIN TRIGLYCERIDES; .ALPHA.-TOCOPHEROL ACETATE; CARNAUBA WAX; TOCOPHEROL; SOYBEAN OIL; GLYCERYL CAPRYLATE; LEVOMENOL; ISOSTEARIC ACID; GLYCERYL 1-UNDECYLENATE

Sun Bum Signature SPF 30 Sunscreen Lip Balm

Active Ingredients

Zinc oxide 8%

Purpose

Sunscreen

Uses

- helps prevent sunburn.
- if used as directed with other sun protection measures, (see Directions) decreases the risk of skin cancer and early skin aging caused by the sun.

Warnings

For external use only.

Do not use

on damaged or broken skin.

When using this product

keep out of eyes. Rinse with water to remove.

Stop use and ask a doctor

if rash occurs.

Keep out of reach of children .

If swallowed, get medical help or contact a Poison Control Center immediately.

Directions

- apply liberally 15 minutes before sun exposure.
- reapply:
- after 80 minutes of swimming or sweating.
- immediately after towel drying.
- at least every 2 hours.
- children under 6 months of age: ask a doctor.
- Sun Protection Measures Spending time in the sun increases your risk of skin cancer and early skin aging, To decrease this risk, regularly use a sunscreen with a Broad Spectrum SPF of 15 or higher and other sun protection measures, including:
- limit time in the sun, especially from 10 a.m. - 2 p.m.
- wear long-sleeved shirts, pants, hats, and sunglasses.

Other Information

Protect this product from excessive heat and direct sun.

Inactive Ingredients

prunus amygdalus dulcis (sweet almond) oil, simmondsia chinensis (jojoba) seed oil, butyrospermum parkii (shea) butter, cera alba (beeswax), euphorbia cerifera (candelilla) wax, argania spinosa kernel (argan) oil, caprylic/capric triglyceride, tocopheryl acetate, copernicia cerifera (carnauba) wax, tocopherol, glycine soja (soybean) oil, glyceryl caprylate, bisabolol, polyhydroxystearic acid, polyglyceryl-3-polyricinoleate, isostearic acid, lecithin, glyceryl undecylenate

Questions or Comments?

Call +1 (877) 978-6286